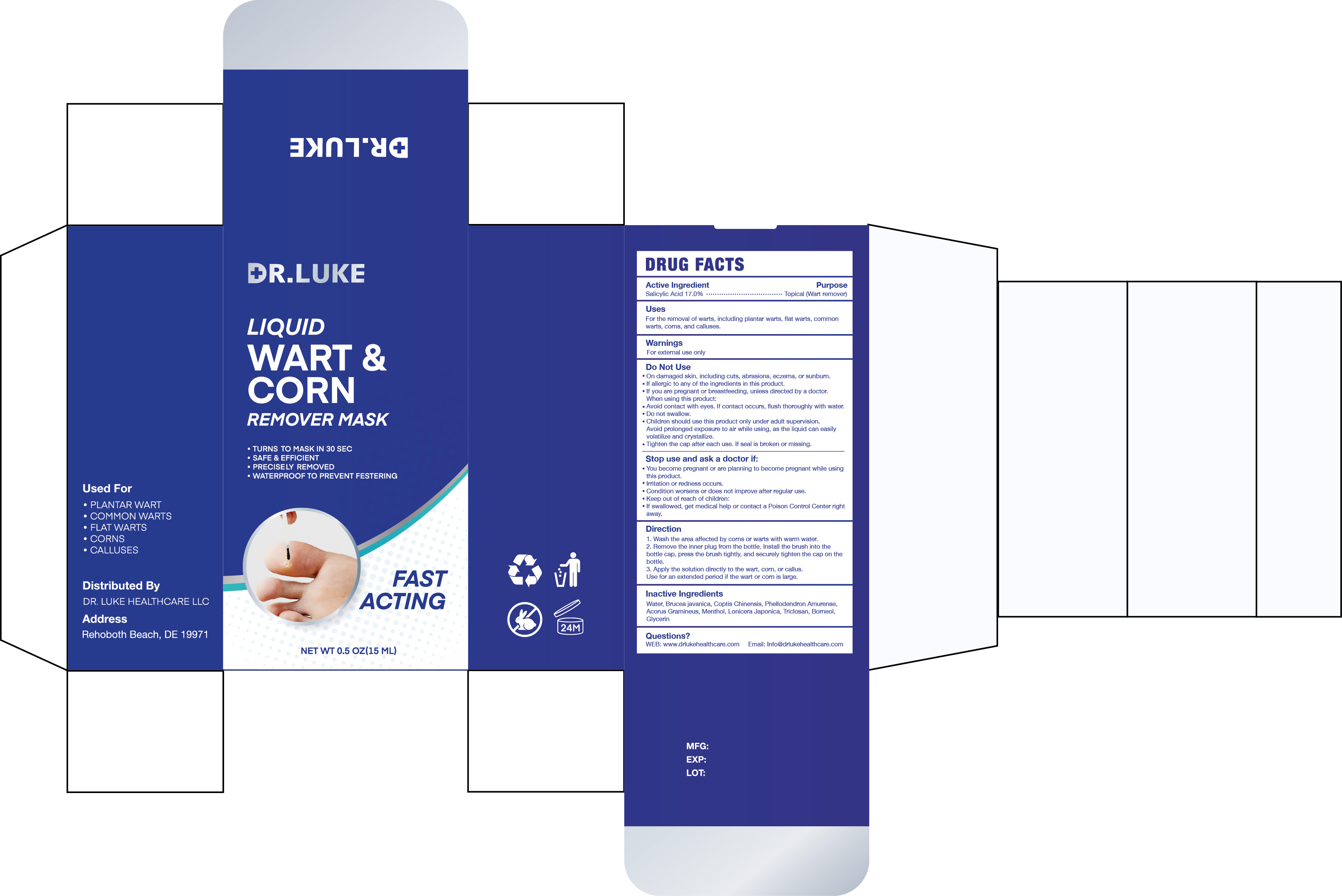 DRUG LABEL: DR.Luke Liquid Wart Remover Mask
NDC: 84746-004 | Form: LIQUID
Manufacturer: Shandong Yuyaotang Pharmaceutical Co., Ltd
Category: otc | Type: HUMAN OTC DRUG LABEL
Date: 20240927

ACTIVE INGREDIENTS: SALICYLIC ACID 17 g/100 mL
INACTIVE INGREDIENTS: WATER; COPTIS CHINENSIS WHOLE; TRICLOSAN; LONICERA JAPONICA WHOLE; BORNEOL; PHELLODENDRON AMURENSE BARK; MENTHOL; BRUCEANTIN; JAVANICIN; ACORUS GRAMINEUS WHOLE; GLYCERIN

84746-004

Active Ingredient

Salicylic Acid 17%

Purpose

Topical (Wart remover)

Use

For the removal of warts, including plantar warts, flat warts, common
warts, corns, and calluses.

Warnings

For external use only.

Do not use

On damaged skin, including cuts, abrasions, eczema, or sunburn.
If allergic to any of the ingredients in this product.
If you are pregnant or breastfeeding, unless directed by a doctor.
Avoid contact with eyes. If contact occurs, flush thoroughly with water.

When Using

Do not swallow.
Children should use this product only under adult supervision.
Avoid prolonged exposure to air while using, as the liquid can easily
volatilize and crystallize.
Tighten the cap after each use. If seal is broken or missing.

Stop Use

You become pregnant or are planning to become pregnant while using this product.
Irritation or redness occurs.
Condition worsens or does not improve after regular use.
Keep out of reach of children:
If swallowed, get medical help or contact a Poison Control Center right away.

Keep Oot Of Reach Of Children

Directions

1. Wash the area affected by corns or warts with warm water.
2. Remove the inner plug from the bottle. Install the brush into the
bottle cap, press the brush tightly, and securely tighten the cap on the
bottle.
3. Apply the solution directly to the wart, corn, or callus.
Use for an extended period if the wart or corn is large.

Inactive ingredients

Water, Brucea javanica, Coptis Chinensis, Phellodendron Amurense, Acorus Gramineus, Menthol, Lonicera Japonica, Triclosan, Borneol, Glycerin

Questions

WEB: www.drlukehealthcare.com

Email: Info@drlukehealthcare.com